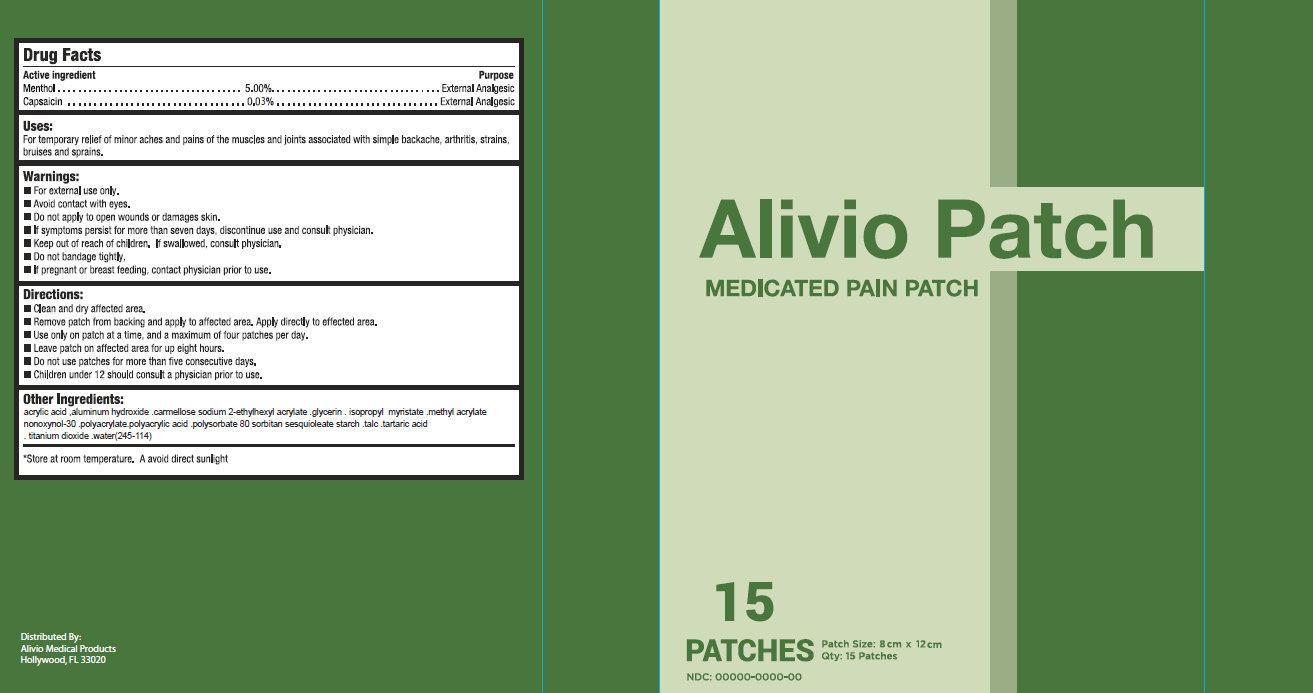 DRUG LABEL: Alivio Medicated Pain
NDC: 69512-001 | Form: PATCH
Manufacturer: Alivio Medical Products, LLC
Category: otc | Type: HUMAN OTC DRUG LABEL
Date: 20150121

ACTIVE INGREDIENTS: MENTHOL 5 g/100 g; CAPSAICIN .03 g/100 g
INACTIVE INGREDIENTS: ACRYLIC ACID; ALUMINUM HYDROXIDE; CROSCARMELLOSE SODIUM; 2-ETHYLHEXYL ACRYLATE; GLYCERIN; ISOPROPYL MYRISTATE; METHYL ACRYLATE; NONOXYNOL-30; POLYACRYLAMIDE (10000 MW); POLYACRYLIC ACID (250000 MW); POLYSORBATE 80; TALC; TARTARIC ACID; TITANIUM DIOXIDE; WATER

Alivio Medicated Pain Patch

Active ingredient

Menthol 5.00%

Capsacin 0.03%

Purpose

External Analgesic

External Analgesic

Uses:

For temporary relief of minor aches and pains of the muscles and joints associated with simple backache, arthritis, strains, bruises and sprains.

Warnings:

- For external use only.
- Avoid contact with eyes.

Do not

- apply to open wounds or damages skin.
- bandage tightly
- If symptoms persist for more than seven days, discontinue use and consult physician.

Keep out of reach of children

If swallwed, consult physician.

If pregnant or breast feeding,

contact physician prior to use.

Directions:

- Clean and dry affected area.
- Remove patch from backing and apply to affected area. Apply directly to effected area.
- Use only on patch at a time, and a maximum of four patches per day.
- Leave patch on affected area for up eight hours.
- Do not use patches for more than five consecutive days.
- Children under 12 should consult a physician prior to use.

Other Ingredients:

acrylic acid ,aluminum hydroxide .carmellose sodium 2-ethylhexyl acrylate .glycerin . isopropyl myristate .methyl acrylate

nonoxynol-30 .polyacrylate.polyacrylic acid .polysorbate 80 sorbitan sesquioleate starch .talc .tartaric acid. titanium dioxide. water (245-114)

Store

at room temperature. Avoid direct sunlight

Package Label

Alivio Patch

MEDICATED PAIN PATCH

15 PATCHES

Distributed by:

Alivio Medical Products

Hollywood, FL 33020